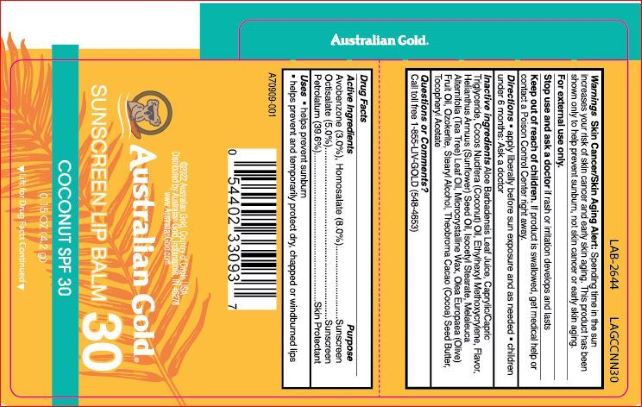 DRUG LABEL: Australian Gold SPF 30 Lip Balm
NDC: 84061-125 | Form: STICK
Manufacturer: Australian Gold
Category: otc | Type: HUMAN OTC DRUG LABEL
Date: 20260121

ACTIVE INGREDIENTS: PETROLATUM 396 mg/1 g; AVOBENZONE 30 mg/1 g; HOMOSALATE 80 mg/1 g; OCTISALATE 50 mg/1 g
INACTIVE INGREDIENTS: CERESIN 165 mg/1 g; CAPRYLIC/CAPRIC/LAURIC TRIGLYCERIDE 120 mg/1 g; ISOCETYL STEARATE 23 mg/1 g

Drug Facts

Active ingredient

Avobenzone, Homosalate, Octisalate, Petrolatum

Purpose

Sunscreen, Skin Protectant

Keep Out of Reach of Children

If swallowed get medical help or contact a Poison Control Center right away.

Uses

Helps prevent sunburn. Helps prevent and temporarily protects dry, chapped or windburned lips.

Warnings

Skin Cancer/Skin Aging Alert: Spending time in the sun increases your risk of skin cancer and early skin aging. This product has been shown only to prevent sunburn, not skin cancer or early aging.

For external use only

Stop use and ask a doctor: If rash or irritation develops and lasts.

Directions

Apply liberally before sun exposure and as needed.

Children under 6 months of age: Ask a doctor before use.